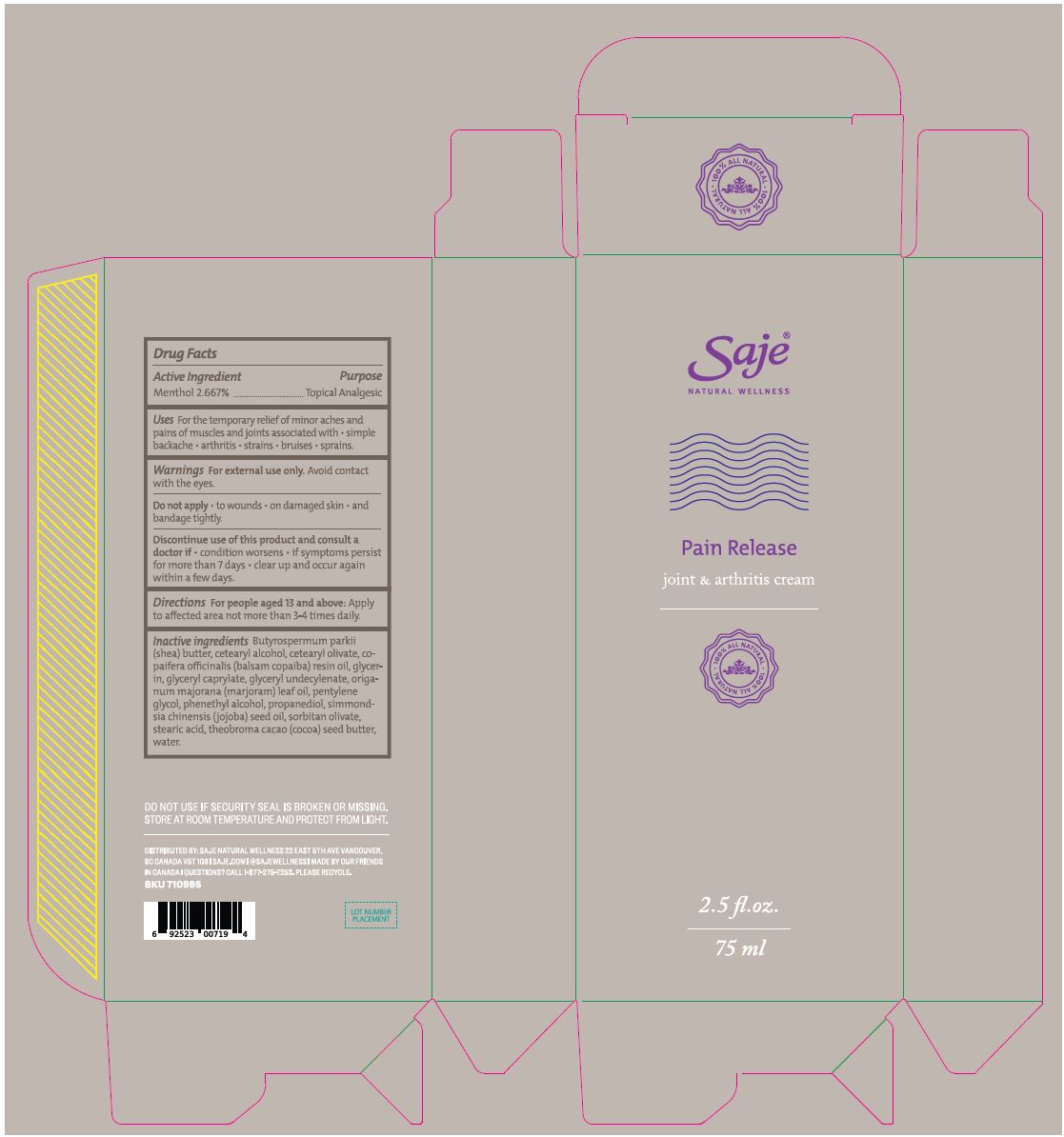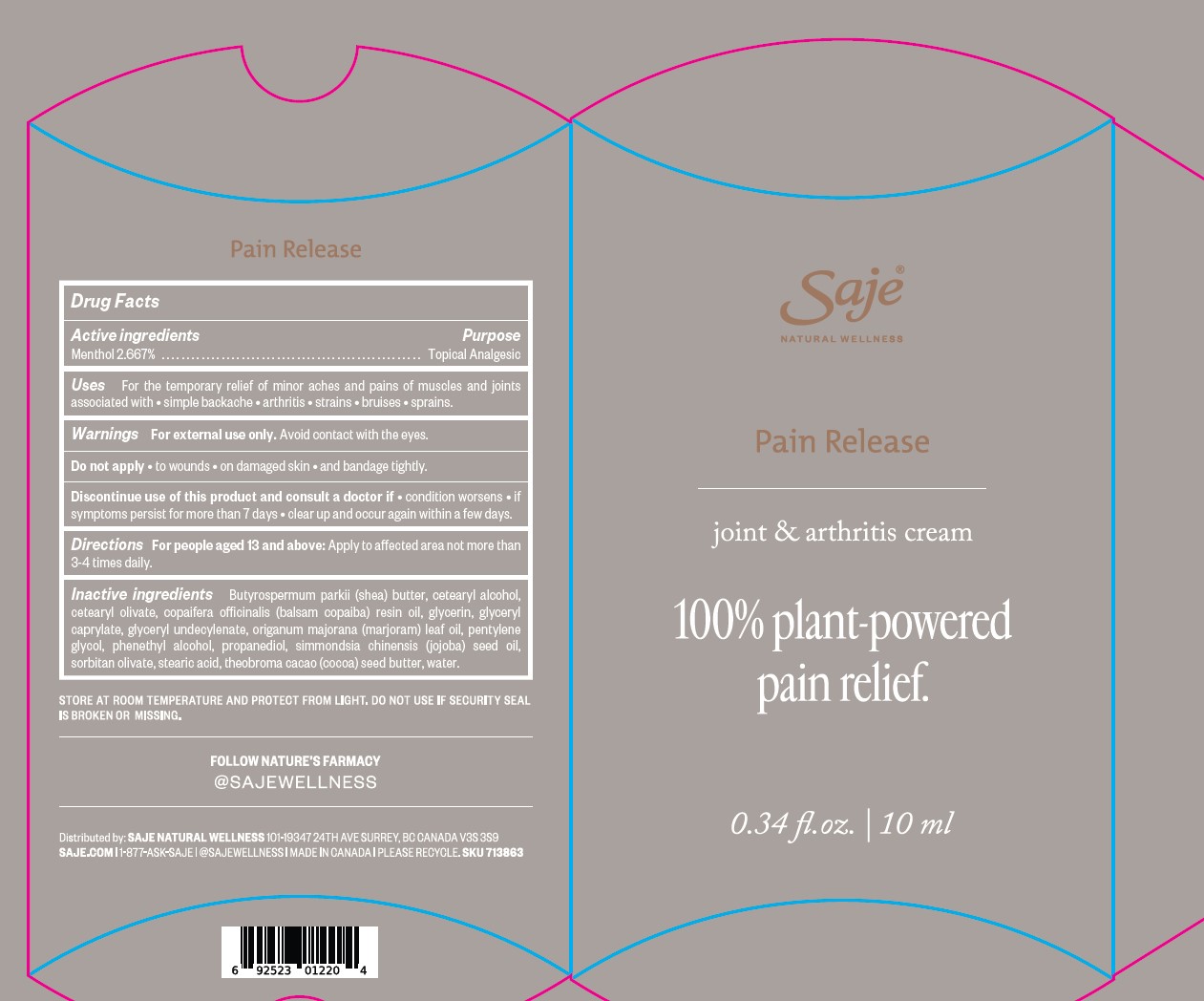 DRUG LABEL: Pain Release Joint and Arthritis Cream
NDC: 70983-028 | Form: CREAM
Manufacturer: Saje Natural Business Inc.
Category: otc | Type: HUMAN OTC DRUG LABEL
Date: 20260113

ACTIVE INGREDIENTS: MENTHOL 2.667 g/100 g
INACTIVE INGREDIENTS: UNDECYLENIC ACID; ORIGANUM MAJORANA; PROPANEDIOL; SORBITAN OLIVATE; COPAIFERA OFFICINALIS RESIN OIL; PHENYLETHYL ALCOHOL; GLYCERYL MONOCAPRYLATE; SHEA BUTTER; COCOA BUTTER; SIMMONDSIA CHINENSIS SEED; PENTYLENE GLYCOL; CETOSTEARYL ALCOHOL; CETEARYL OLIVATE; WATER; GLYCERIN; STEARIC ACID

ACTIVE INGREDIENT

Menthol 2.667%

PURPOSE

topical analgesic

INDICATIONS AND USAGE

For the temporary relief of minor aches and pains of muscles and joints associated with • simple backache • arthritis • strains • bruises • sprains

Keep out of reach of children

DOSAGE AND ADMINISTRATION

Directions For people aged 13 and above: Apply to affected area not more than 3-4 times daily.

STORAGE AND HANDLING

Store at room temperature and protect from light.

INACTIVE INGREDIENT

Inactive Ingredients Butyrospermum parkii (shea) butter, cetearyl alcohol, cetearyl olivate, copaifera officinalis (balsam copaiba) resin oil, glycerin, glyceryl caprylate, glyceryl undecylenate, origanum majorana (marjoram) leaf oil, pentylene glycol, phenethyl alcohol, propanediol, simmondsia chinensis (jojoba) seed oil, sorbitan olivate, stearic acid, theobroma cacao (cocoa) seed butter, water.

Warnings
For external use only. Avoid contact with the eyes. Do not apply • to wounds • on damaged skin • and bandage tightly. Discontinue use of this product and consult a doctor if • condition worsens • if symptoms persist for more than 7 days • clear up and occur again within a few days.

STOP USE

Discontinue use of this product and consult a doctor if • condition worsens • if symptoms persist for more than 7 days • clear up and occur again within a few days.

DO NOT USE

Do not apply • to wounds • on damaged skin • and bandage tightly.

WHEN USING

For external use only. Avoid contact with the eyes.